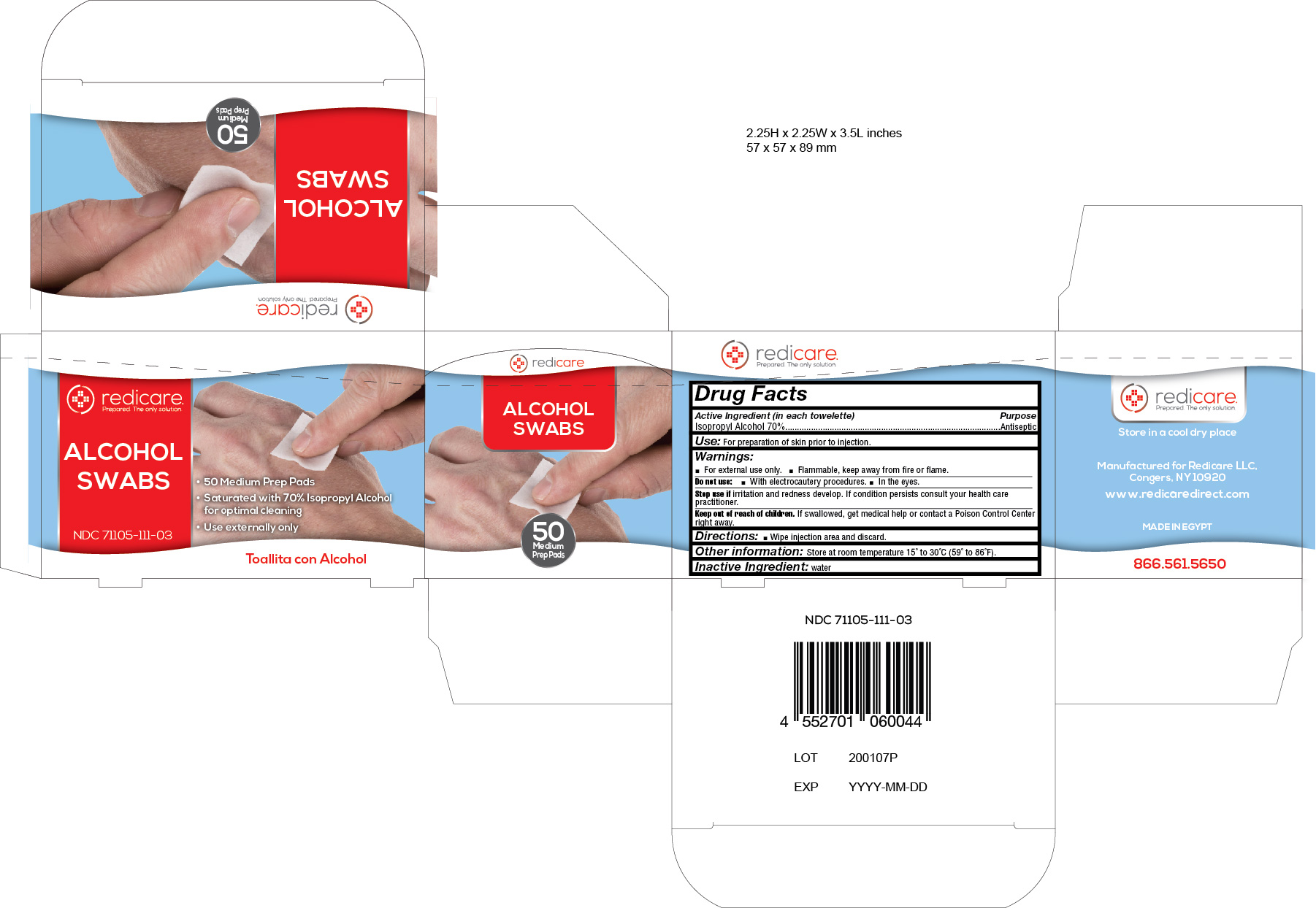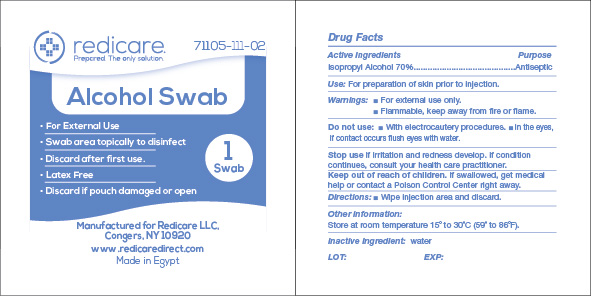 DRUG LABEL: Alcohol Pad
NDC: 71105-111 | Form: SWAB
Manufacturer: Redicare LLC
Category: otc | Type: HUMAN OTC DRUG LABEL
Date: 20191211

ACTIVE INGREDIENTS: ISOPROPYL ALCOHOL 70 g/100 g
INACTIVE INGREDIENTS: WATER

Alcohol Prep Pads

Active Ingredient (in each towelette) ............Purpose

Isopropyl Alcohol 70%..........Antiseptic

Use:

For preparation of skin prior to injection.

Warnings:

- For external use only
- Flammable, keep away from fire or flame.

Do not use:

- With electrocautery procedures
- In the eyes

Stop use if

irritation and redness develop. If condition persists consult your health care practitioner.

Keep out of reach of children.

If swallowed, get medical help or contact a Poison COntrol Center right away.

Directions:

Wipe injection area and discard.

Other information:

Store at room temperature 15o to 30oC (59o to 86oF).

Inactive ingredient:

water